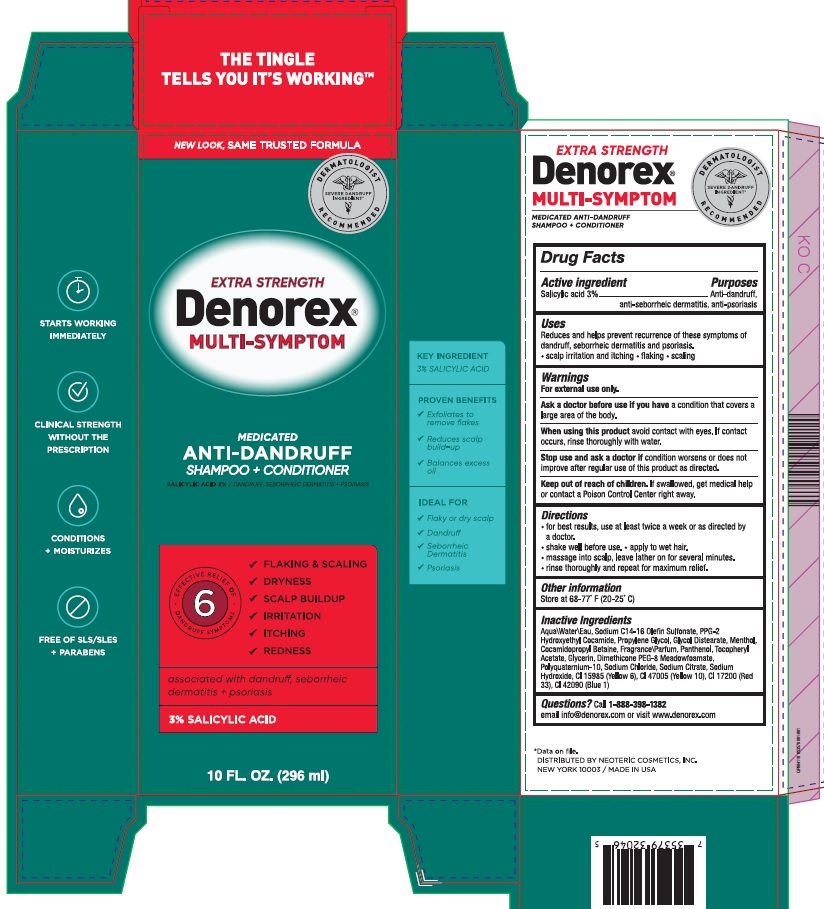 DRUG LABEL: Denorex Extra Strength
NDC: 62673-059 | Form: SHAMPOO
Manufacturer: Neoteric Cosmetics, Inc.
Category: otc | Type: HUMAN OTC DRUG LABEL
Date: 20250429

ACTIVE INGREDIENTS: SALICYLIC ACID 0.03 g/1 mL
INACTIVE INGREDIENTS: SODIUM HYDROXIDE; DIMETHICONE PEG-8 MEADOWFOAMATE; SODIUM CHLORIDE; WATER; SODIUM C14-16 OLEFIN SULFONATE; PROPYLENE GLYCOL; GLYCOL DISTEARATE; MENTHOL; COCAMIDOPROPYL BETAINE; PANTHENOL; .ALPHA.-TOCOPHEROL ACETATE; SODIUM CITRATE; FD&C YELLOW NO. 6; D&C YELLOW NO. 10; D&C RED NO. 33; FD&C BLUE NO. 1; GLYCERIN; POLYQUATERNIUM-10 (10000 MPA.S AT 2%); PPG-2 HYDROXYETHYL COCAMIDE

Denorex Extra Strength with Conditioner

Drug Facts

Active ingredient

Salicylic acid 3%

Purpose

Anti-dandruff, anti-seborrheic dermatitis, anti-psoriasis

Uses

Reduces and helps prevent recurrence of these symptoms of dandruff, seborrheic dermatitis and psoriasis.

• scalp irritation and itching • flaking • scaling

Warnings

For external use only.

Ask a doctor before use if you have

a condition that covers a large area of body.

When using this product

avoid contact with eyes. If contact occurs, rinse thoroughly with water.

Stop use and ask a doctor

If condition worsens or does not improve after regular use of this product as directed.

Keep out of reach of children

If swallowed, get medical help or contact a Poison Control Center right away.

Directions

- for best results, use at least twice a week or as directed by a doctor.
- shake well before use. • apply to wet hair.
- massage into scalp, leave lather on for several minutes.
- rinse thoroughly and repeat for maximum relief.

Other information

Store at 68-77° F (20-25° C)

Inactive ingredients

Aqua\Water\Eau, Sodium C14-16 olefin sulfonate, PPG-2 Hydroxyethyl Cocamide, Propylene glycol, Glycol distearate, Menthol, Cocamidopropyl betaine, Fragrance\Parfum, Panthenol, Tocopheryl acetate, Glycerin, Dimethicone PEG-8 Meadowfoamate, Polyquaternium-10, Sodium chloride, Sodium citrate, Sodium hydroxide, CI 15985 (Yellow 6), CI 47005 (Yellow 10), CI 17200 (Red 33), CI 42090 (Blue 1)

Questions?

Call 1-888-398-1382

email info@denorex.com or visit www.denorex.com

EXTRA STRENGTH

Denorex®

MULTI-SYMPTOM

MEDICATED ANTI-DANDRUFF

SHAMPOO + CONDITIONER

DISTRIBUTED BY NEOTERIC COSMETICS, INC.

NEW YORK 10003 / MADE IN USA

PRINCIPAL DISPLAY PANEL

EXTRA STRENGTH

Denorex®

MULTI-SYMPTOM

MEDICATED

ANTI-DANDRUFF

SHAMPOO + CONDITIONER

SALICYLIC ACID 3% / DANDRUFF, SEBORRHEIC DEMATITIS + PSORIASIS

EFFECTIVE RELIEF OF 6 DANDRUFF SYMPTOMS

FLAKING & SCALING

DRYNESS

SCALP BUILDUP

IRRITATION

ITCHING

REDNESS

associated with dandruff, seborrheic dermatitis + psoriasis

3% SALICYLIC ACID

10 FL OZ. (296 ml)